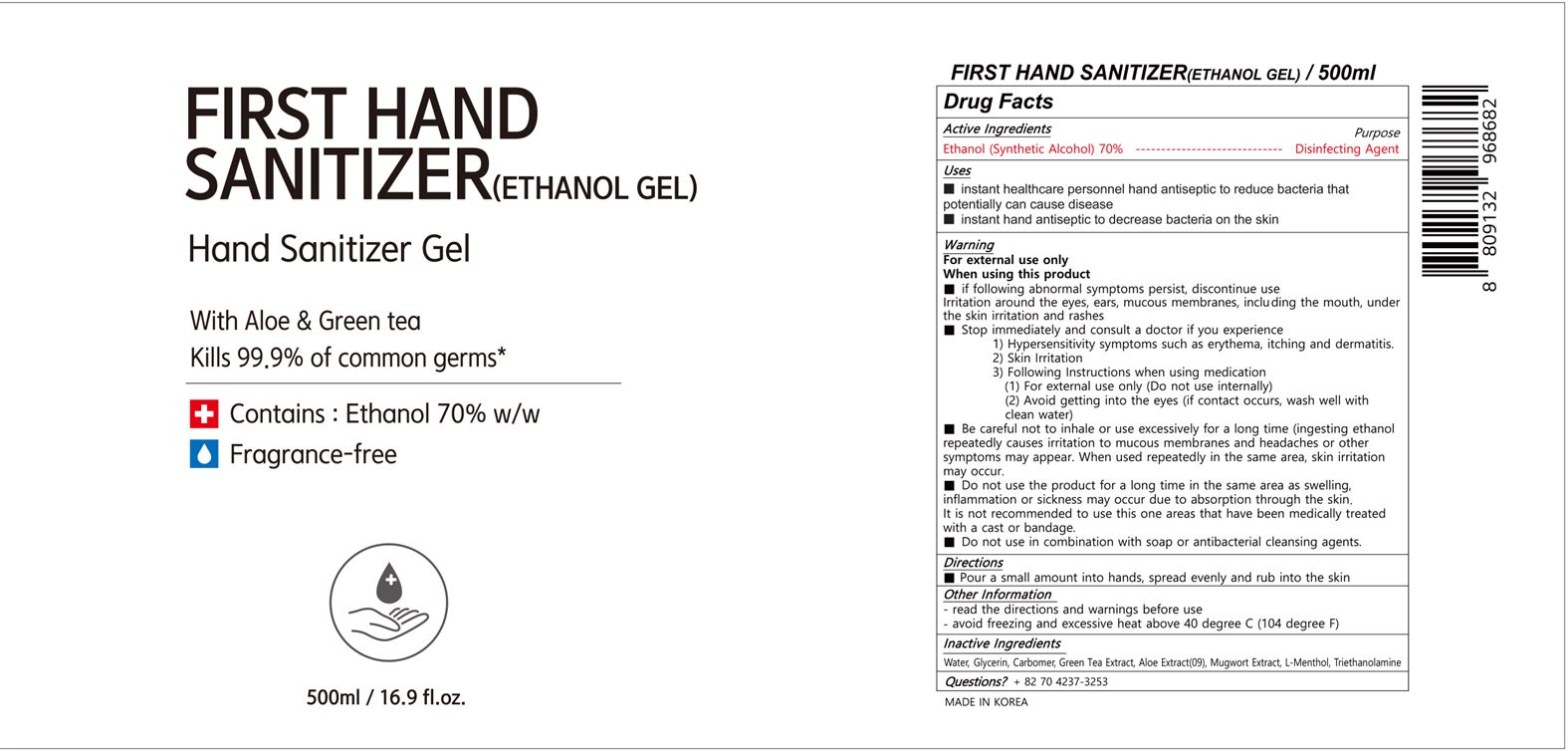 DRUG LABEL: FIRST HAND SANITIZER
NDC: 74406-001 | Form: GEL
Manufacturer: Korea Life Science Co.,ltd
Category: otc | Type: HUMAN OTC DRUG LABEL
Date: 20200518

ACTIVE INGREDIENTS: ALCOHOL 248 mL/400 mL
INACTIVE INGREDIENTS: GLYCERIN; GREEN TEA LEAF; ARTEMISIA PRINCEPS LEAF; WATER; CARBOMER HOMOPOLYMER, UNSPECIFIED TYPE; LEVOMENTHOL

ACTIVE INGREDIENT

ALCOHOL

INACTIVE INGREDIENT

glycerin carbomer, green tea extract, aloe extract, mugwort extract, L-menthol, triethanolamine

PURPOSE

SANITIZER

WARNINGS

1.Do not use the product on the following areas:

Around the eyes and ears, in the mouth, large body parts and damaged skin(Irritation may occur)

2.If you experience any of the following symptoms, discontinue use of the product immediately and consult a physician or pharmacist.
1) Hypersensitivity symptoms, e.g. rash, erythema, itchiness, and edema
2)Skin irritation symptoms

3.Other precautions
1) For external use only (do not swallow).
2) Avoid contact with eyes. If contact occurs, wash with clean water and consult a doctor or pharmacist.
3)Be careful not to inhale vapors in cases of extended or prolonged use. (Repeating inhaling of large amounts of ethanol vapor may cause irritation of the mucous membranes and headaches).

Keep out of reach of children and go to the hospital immediately if swallowed.

Uses

Disinfection of hands and skin

Directions

Take an appropriate amount on your hands and rub thoroughly to dry.